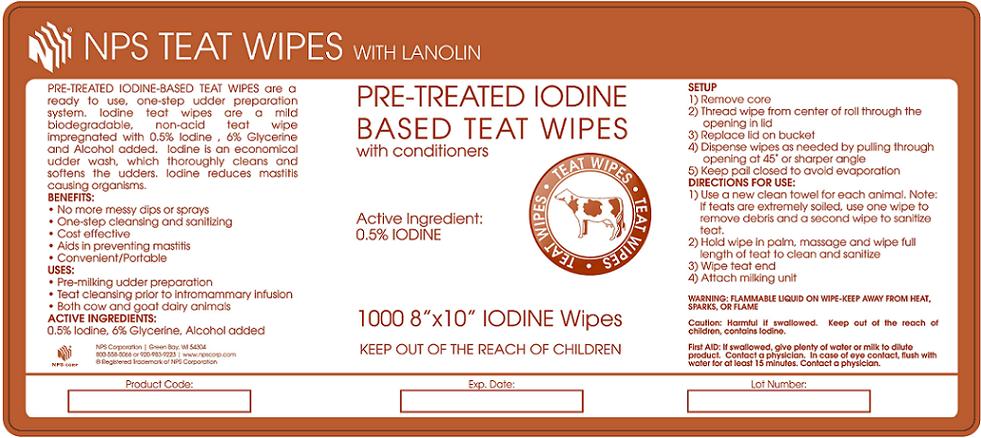 DRUG LABEL: NPS IODINE TEAT WIPES WITH LANOLIN
								
NDC: 67313-4300 | Form: LIQUID
Manufacturer: National Packaging Services (NPS Corp)
Category: animal | Type: OTC ANIMAL DRUG LABEL
Date: 20130404

ACTIVE INGREDIENTS: IODINE 100.244 g/3.785 L
INACTIVE INGREDIENTS: Glycerin 1202.93 g/3.785 L

NPS Teat Wipes with Lanolin Pre-Treated Iodine based Teat Wipes with Conditioner

DESCRIPTION

PRE-TREATED IODINE BASED TEAT WIPES are a ready to use, one step udder preparation system. Iodine teat wipes are a mild, biodegradable non-acid, teat wipe impregnated with 0.5% Iodine, 6% Glycerine and Alcohol added. Iodine is an economical udder wash, which thoroughly cleans and softens the udder. Iodine reduces mastitis causing organisms.

BENEFITS:

- No more messy dips or sprays
- One-step cleaning and sanitizing
- Cost effective
- Aids in preventing mastitis
- Convenient/Portable

USES:

- Pre-milking udder preparation
- Teat cleansing prior to intromammory infusion
- Both cow and goat dairy animals

Ingredients:

1. .5% Iodine (Active Ingredient)
2. 6% Glycerin
3. Alcohol added

Setup:

1. Remove core
2. Thread wipe from center of roll through the opening in the lid
3. Replace lid on bucket.
4. Dispense wipes as needed by needed, by pulling through opening at 45 degree or sharper angle.
5. Keep pail closed to avoid evaporation.

Directions for Use:

1. Use a clean towel for each animal. Note: If teats are extremely soiled, use one wipe to remove debris and a second wipe to sanitize teat.
2. Hold wipe in palm, massage and wipe full length of teat to clean and sanitize.
3. Wipe teat end.
4. Attach milking unit.

Warning:

WARNING: FLAMMABLE LIQUID ON WIPE, KEEP AWAY FROM HEAT, SPARKS OR FLAME.

Caution: Harmful if swallowed. Keep out of the reach of children, contains Iodine.

First Aid: If swallowed, give plenty of water or milk to dilute product. Contact a physician. In case of eye contact, flush with water for at least 15 minutes. Contact a physician.

PACKAGE LABEL

NPS1